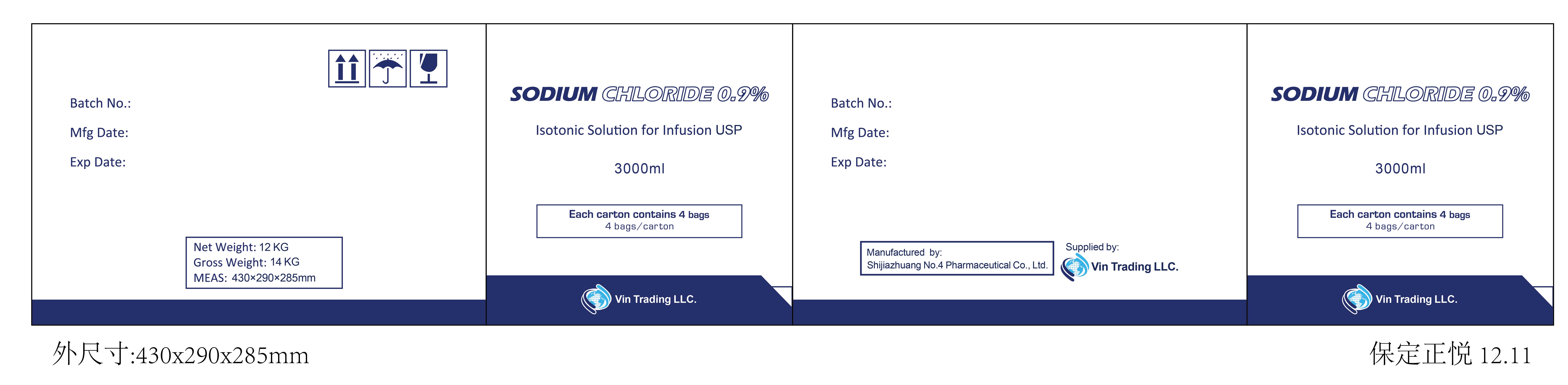 DRUG LABEL: Sodium Chloride
NDC: 85036-300 | Form: INJECTION, SOLUTION
Manufacturer: Vin TRADING LLC
Category: prescription | Type: HUMAN PRESCRIPTION DRUG LABEL
Date: 20241227

ACTIVE INGREDIENTS: SODIUM CHLORIDE 27 g/3000 mL

COMPONENTS

1000ml

SODIUM CHLORIDE 0.9%

Isotonic Solution for Infusion UPS

Composition:

Each 100ml contains...0.9% (m/v-w/v)

Water for Injection..........................q.s.

Electrolytes (mEq/liter)

Na+ 150 CI 150

BATCH NO:

MFG DATE:

EXP. DATE:

Supplied by:

Vin Trading LLC

USER SAFETY WARNINGS

Caution:

FOR INTRAVENOUS INFUSION ONLY

Not to be used if container is found leaking or solution is not clear.

Solution containing visible solid particles should not be used.

Any portion of the contents remaining should be discarded.

For use under medical supervision.

STORAGE AND HANDLING

Sterile, nonpyrogenic, Single unit container. Discard unused portion.

Recommended storage. Store at 20-25*C (66-77*F)

Avoid excessive heat. Protect from freezing

PACKAGE LABEL

Carton3000ml.jpg